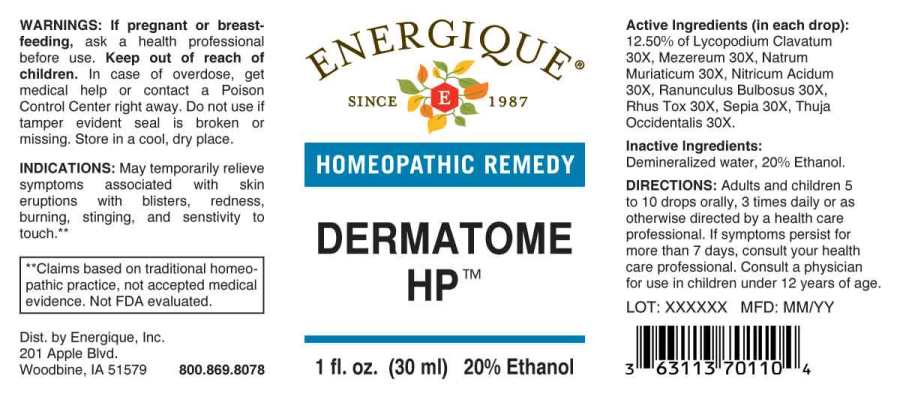 DRUG LABEL: DERMATOME HP
NDC: 44911-0569 | Form: LIQUID
Manufacturer: Energique, Inc.
Category: homeopathic | Type: HUMAN OTC DRUG LABEL
Date: 20241024

ACTIVE INGREDIENTS: LYCOPODIUM CLAVATUM SPORE 30 [hp_X]/1 mL; DAPHNE MEZEREUM BARK 30 [hp_X]/1 mL; SODIUM CHLORIDE 30 [hp_X]/1 mL; NITRIC ACID 30 [hp_X]/1 mL; RANUNCULUS BULBOSUS 30 [hp_X]/1 mL; TOXICODENDRON PUBESCENS LEAF 30 [hp_X]/1 mL; SEPIA OFFICINALIS JUICE 30 [hp_X]/1 mL; THUJA OCCIDENTALIS LEAF 30 [hp_X]/1 mL
INACTIVE INGREDIENTS: WATER; ALCOHOL

DRUG FACTS:

ACTIVE INGREDIENTS:

(in each drop): 12.50% of Lycopodium Clavatum 30X, Mezereum 30X, Natrum Muriaticum 30X, Nitricum Acidum 30X, Ranunculus Bulbosus 30X, Rhus Tox 30X, Sepia 30X, Thuja Occidentalis 30X.

INDICATIONS:

May temporarily relieve symptoms associated with herpetic eruptions, such as rashes and cold sores.**

**Claims based on traditional homeopathic practice, not accepted medical evidence. Not FDA evaluated.

WARNINGS:

If pregnant or breast-feeding, ask a health professional before use.

Keep out of reach of children. In case of overdose, get medical help or contact a Poison Control Center right away.

Do not use if tamper evident seal is broken or missing. Store in a cool, dry place.

Keep out of reach of children. In case of overdose, get medical help or contact a Poison Control Center right away.

DIRECTIONS:

Adults and children 5 to 10 drops orally, 3 times daily or as otherwise directed by a health care professional. If symptoms persist for more than 7 days, consult your health care professional. Consult a physician for use in children under 12 years of age.

INDICATIONS:

May temporarily relieve symptoms associated with herpetic eruptions, such as rashes and cold sores.**

**Claims based on traditional homeopathic practice, not accepted medical evidence. Not FDA evaluated.

INACTIVE INGREDIENTS:

Demineralized water, 20% Ethanol.

QUESTIONS:

Dist. by Energique, Inc.

201 Apple Blvd

Woodbine, IA 51579 800.869.8078

PACKAGE LABEL DISPLAY:

ENERGIQUE

SINCE 1987

HOMEOPATHIC REMEDY

DERMATOME HP

1 fl. oz. (30 ml)